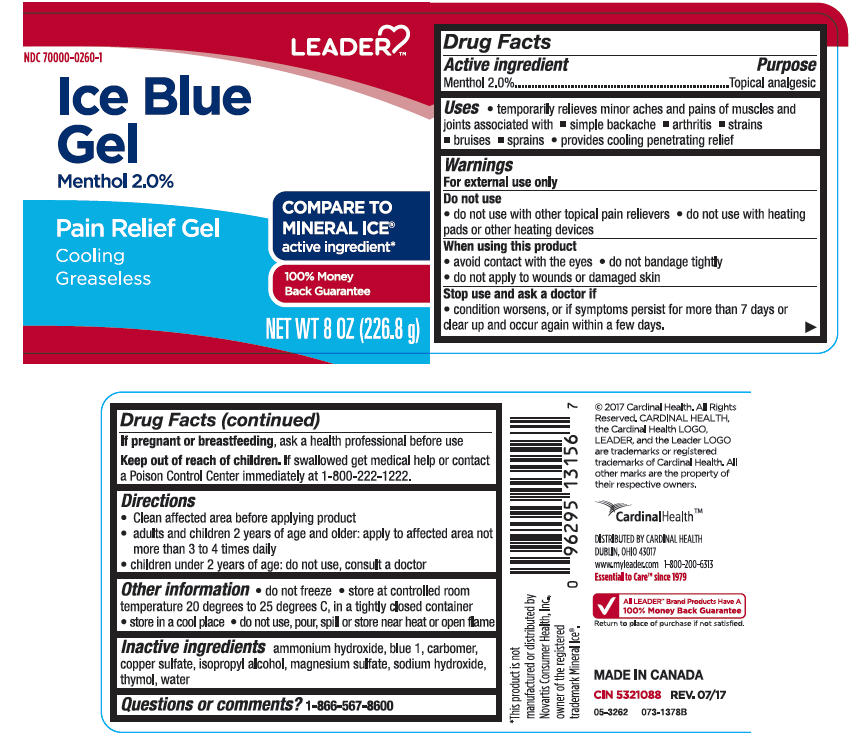 DRUG LABEL: Leader Ice Blue
NDC: 70000-0260 | Form: GEL
Manufacturer: Cardinal Health, 110 dba LEADER
Category: otc | Type: HUMAN OTC DRUG LABEL
Date: 20240209

ACTIVE INGREDIENTS: Menthol, Unspecified Form 20 mg/1 g
INACTIVE INGREDIENTS: AMMONIA; DISODIUM N-ETHYL-N-4-((4-(ETHYL((3-SULFOPHENYL)METHYL)AMINO)PHENYL)(2-SULFOPHENYL)METHYLENE)-2,5-CYCLOHEXADIEN-1-YLIDENE)-3-SULFOBENZENEMETHANAMINIUM; CARBOXYMETHYLCELLULOSE SODIUM, UNSPECIFIED; CUPRIC SULFATE ANHYDROUS; ISOPROPYL ALCOHOL; MAGNESIUM SULFATE ANHYDROUS; SODIUM HYDROXIDE; THYMOL; WATER

Leader Ice Blue Gel
Topical Analgesic

Drug Facts

Active ingredients

Menthol 2%

Purpose

Topical Analgesic

Uses

- temporarily relieves minor aches and pains of muscles and joints associated with
  - simple backache
  - arthritis
  - strains
  - bruises
  - sprains
- provides cooling penetrating relief

Warnings

For external use only

- do not use with other topical pain relievers
- do not use with heating pads or other heating devices

When using this product

- avoid contact with the eyes
- do not bandage tightly
- do not apply to wounds or damaged skin

Stop use and consult a doctor if

- condition worsens, or if symptoms persist for more than 7 days or clear up and occur again within a few days.

PREGNANCY OR BREAST FEEDING

If pregnant or breastfeeding, ask a health professional before use

Keep out of reach of children. If swallowed, get medical help or contact a Poison Control Center immediately at 1-800-222-1222.

Directions

- Clean affected area before applying product
- adults and children 2 years of age and older: apply to affected area not more than 3 to 4 times daily
- children under 2 years of age: do not use, consult a doctor

Other information

- do not freeze
- store at controlled room temperature 20 degrees to 25 degrees C, in a tightly closed container
- store in a cool place
- do not use, pour, spill or store near heat or open flame

Inactive ingredients

Ammonium Hydroxide, Blue 1, Carbomer, Copper Sulfate, Isopropyl Alcohol, Magnesium Sulfate, Sodium Hydroxide, Thymol, Water.

Questions or comments?

1-866-567-8600

DISTRIBUTED BY CARDINAL HEALTH
DUBLIN, OHIO 43017

PRINCIPAL DISPLAY PANEL - 226.8 g Jar Label

LEADER

NDC 70000-0260-1

Ice Blue
Gel
Menthol 2.0%

Pain Relief Gel

Cooling
Greaseless

COMPARE TO
MINERAL ICE®
active ingredient*

100% Money
Back Guarantee

NET WT 8 OZ (226.8 g)